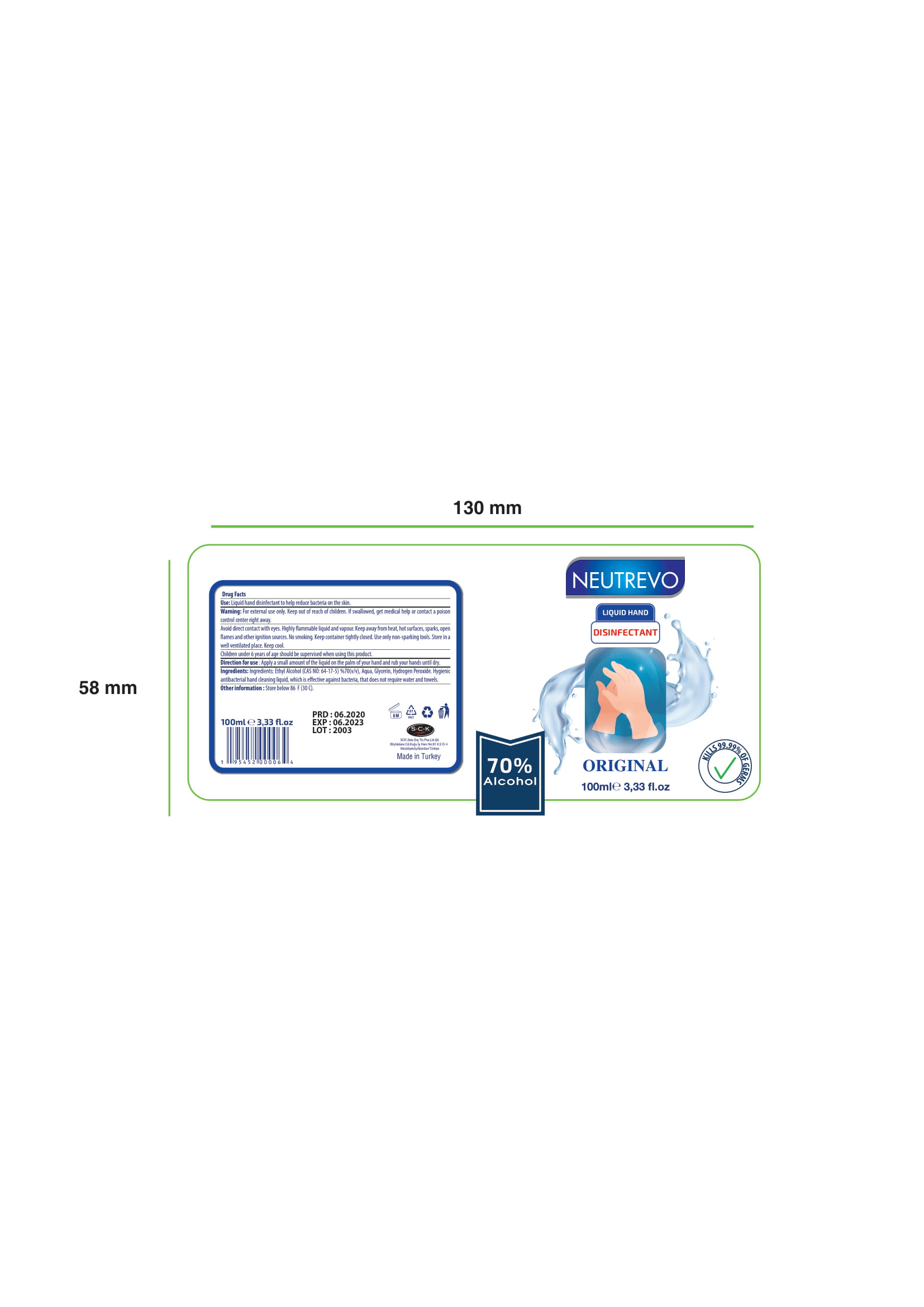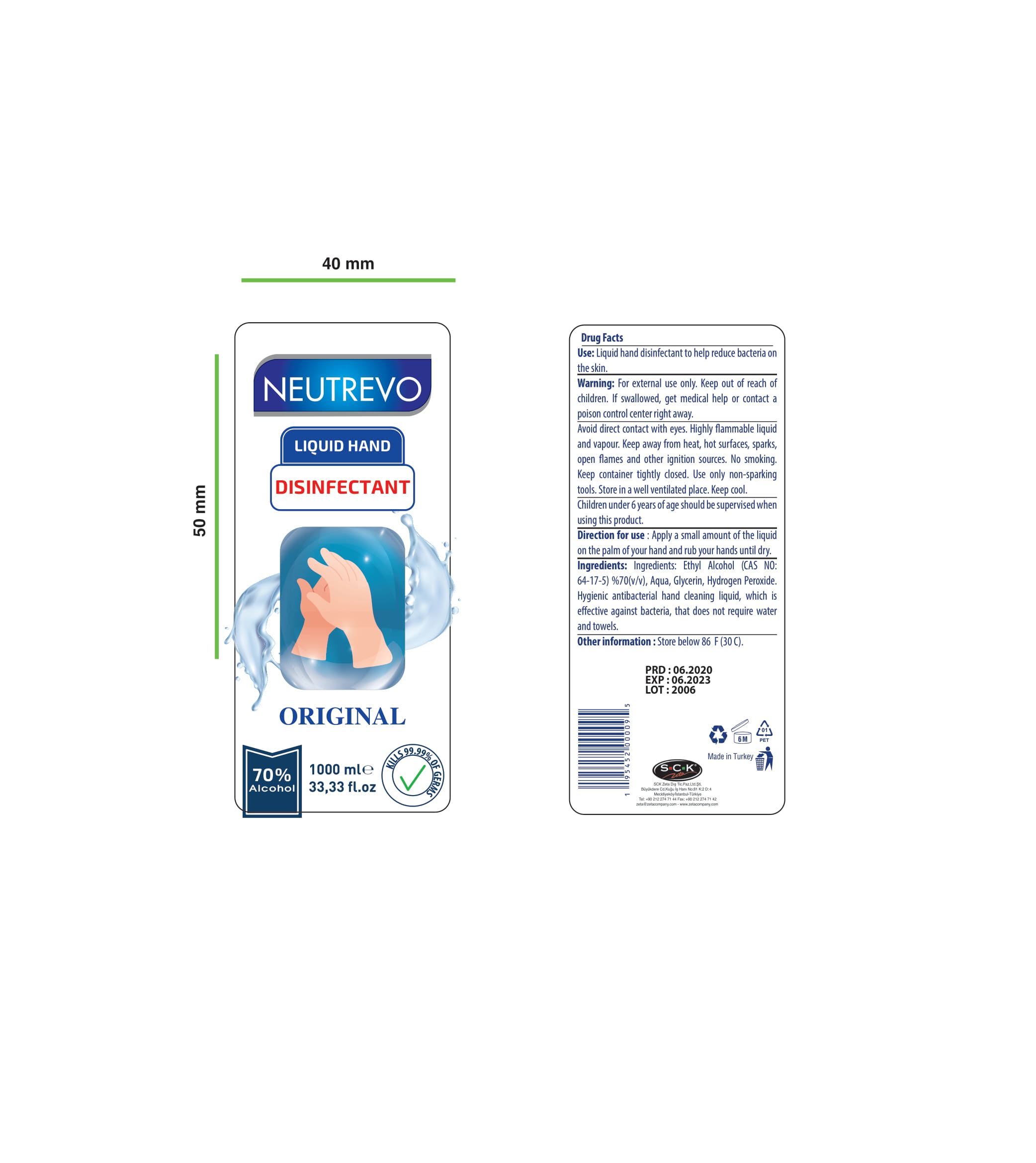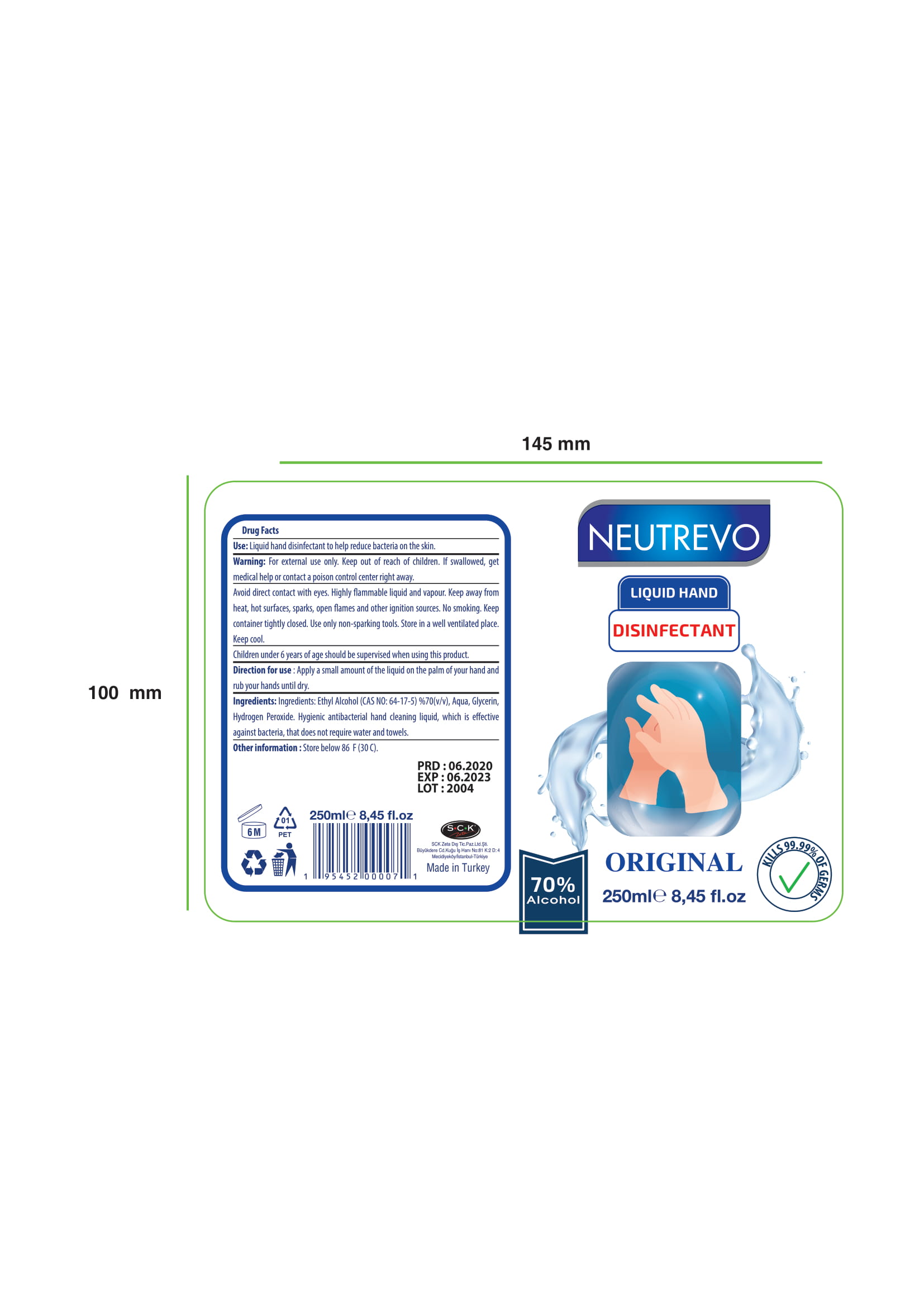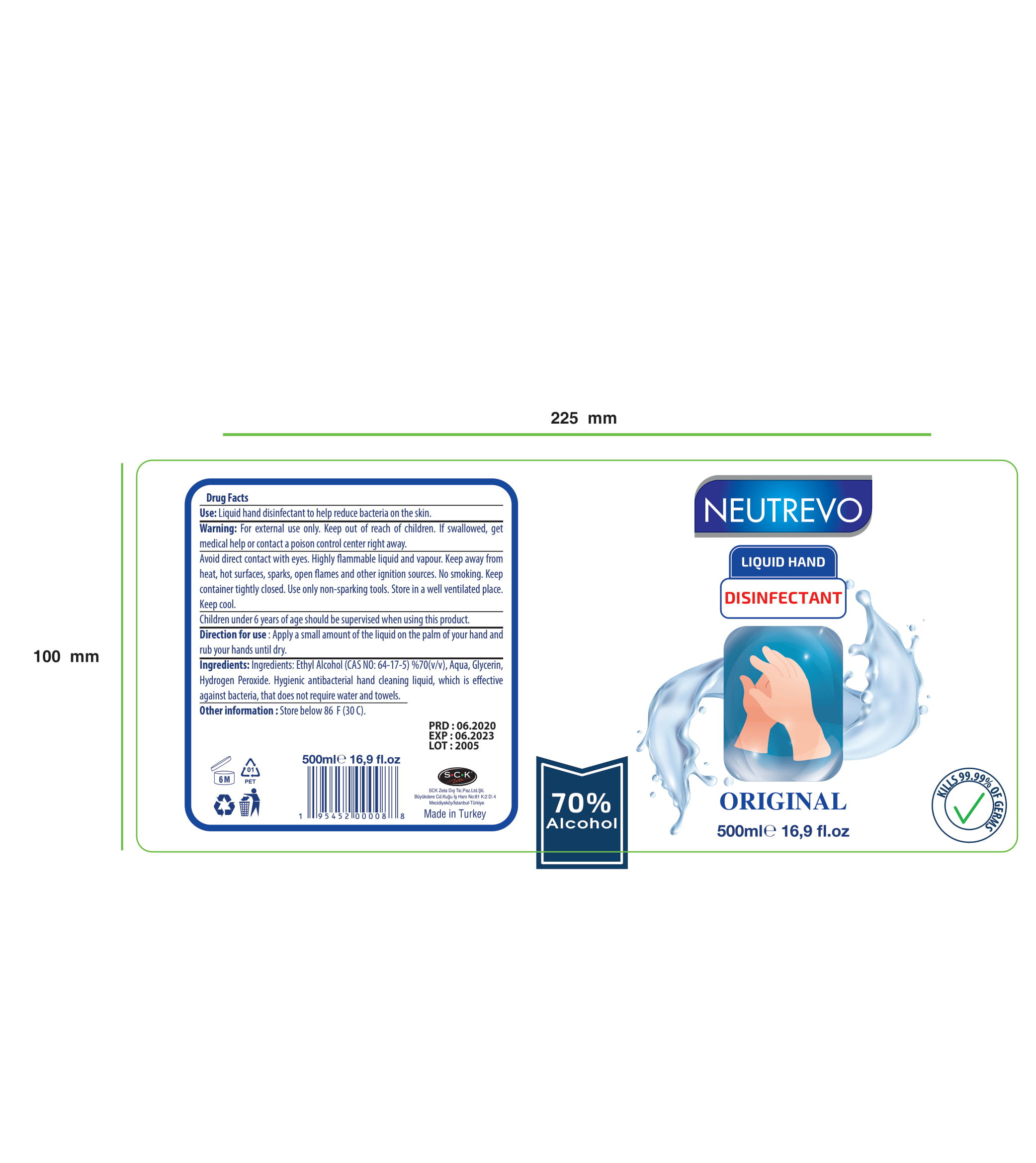 DRUG LABEL: Neutrevo Liquid Hand Disinfectant
NDC: 86818-003 | Form: LIQUID
Manufacturer: SCK ZETA DIS TICARET PAZARLAMA LIMITED SIRKETI
Category: otc | Type: HUMAN OTC DRUG LABEL
Date: 20220123

ACTIVE INGREDIENTS: ALCOHOL 70 mL/100 mL
INACTIVE INGREDIENTS: GLYCERIN; HYDROGEN PEROXIDE; WATER

Neutrevo Liquid Hand Disinfectant

This is a hand sanitizer manufactured according to the Temporary Policy for Preparation of Certain Alcohol-Based Hand Sanitizer Products During the Public Health Emergency (CoViD-19); Guidance for Industry.

The hand sanitizer is manufactured using only the following United States Pharmacopoeia (USP) grade ingredients in the preparation of the product (percentage in final product formulation) consistent with World Health Organization (WHO) recommendations:

1. Alcohol (ethanol) (USP or Food Chemical Codex (FCC) grade) (70%, volume/volume (v/v)) in an aqueous solution denatured according to Alcohol and Tobacco Tax and Trade Bureau regulations in 27 CFR part 20.
2. Glycerol
3. Hydrogen peroxide
4. Sterile distilled water or boiled cold water.

The firm does not add other active or inactive ingredients. Different or additional ingredients may impact the quality and potency of the product.

Active Ingredient(s)

Alcohol 70% v/v. Purpose: Antiseptic

Purpose

Antiseptic, Hand Sanitizer

Use

Liquid hand disinfectant to help reduce bacteria on the skin.

Warnings

For external use only. Flammable. Keep away from heat or flame

Do not use

- in children less than 2 months of age
- on open skin wounds

WHEN USING

Avoid direct contact with eyes. Highly flammable liquid and vapour.

Keep away from heat, hot surfaces, sparks, open flames and other ignition sources. No smoking. Keep container tightly closed. Use only non-sparking tools. Store in a well ventilated place. Keep cool.
Keep out of reach of children. If swallowed, get medical help or contact a Poison Control Center right away.

Stop use and ask a doctor if irritation or rash occurs. These may be signs of a serious condition.

Keep out of reach of children. If swallowed, get medical help or contact a Poison Control Center right away.

Directions

- Apply a small amount of the liquid on the palm of your hand and rub your hands until dry.
- Children under 6 years of age should be supervised when using this product.

Other information

- Store below 86 F (30 C).

Inactive ingredients

glycerin, hydrogen peroxide, purified water USP

Package Label - Principal Display Panel

100 mL NDC: 86818-003-01

250 ml NDC 86818-003-02

500 ml NDC 86818-003-03

1000 ml NDC 86818-003-04